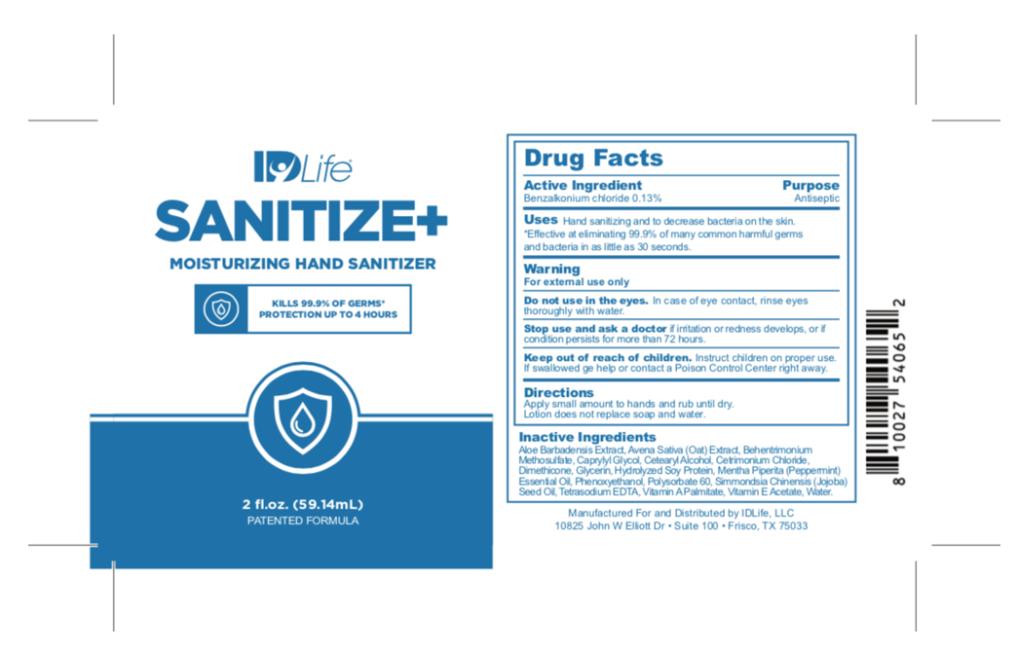 DRUG LABEL: IDLife SANITIZE MOISTURIZING HAND SANITIZER
NDC: 69243-1111 | Form: LOTION
Manufacturer: Willspeed Technologies LLC
Category: otc | Type: HUMAN OTC DRUG LABEL
Date: 20220114

ACTIVE INGREDIENTS: BENZALKONIUM CHLORIDE 0.0013 g/1 mL
INACTIVE INGREDIENTS: ALOE VERA LEAF; AVENA SATIVA LEAF; BEHENTRIMONIUM METHOSULFATE; BUTYLENE GLYCOL; CAPRYLYL GLYCOL; CETRIMONIUM CHLORIDE; DIMETHICONE; GLYCERIN; SOY PROTEIN; PEPPERMINT OIL; PHENOXYETHANOL; VITAMIN A PALMITATE; JOJOBA OIL; SORBIC ACID; EDETATE SODIUM; ALPHA-TOCOPHEROL ACETATE; WATER

IDLife SANITIZE MOISTURIZING HAND SANITIZER

DRUG FACTS

Active Ingredient

Benzalkonium chloride 0.13%

Purpose

Antiseptic

Uses

Kills 99.99 % germs and moisturizes skin.

Warnings

For external use only.

Do not use in the eyes.

In case of eye contact, rinse eyes thoroughly with water.

Stop use and ask a doctor

if irritation or redness develops, or if condition persists more than 72 hours.

Keep out of reach of children.

Instruct children on proper use. If swallowed, get medical help or contact a Poison Control Center right away.

Directions

Apply a small amount to hands and rub until dry. Lotion does not replace soap and water.

Inactive Ingredients

Aloe Barbadensis Extract, Avena Sativa (Oat) Extract, Behentrimonium Methosulfate, Caprylyl Glycol, Cetearyl Alcohol, Cetrimonium Chloride, Dimethicone, Glycerin, Hydrolyzed Soy Protein, Mentha Piperita (Peppermint) Essential Oil, Phenoxyethanol, Polysorbate 60, Simmondsia Chinensis (Jojoba) Seed Oil, Tetrasodium EDTA, Vitamin A Palmitate, Vitamin E Acetate, Water.

PRINCIPAL DISPLAY PANEL

IDLife

SANITIZE+
MOISTURIZING HAND SANITIZER
Kills 99.9% OF GERMS PROTECTION UP TO 4 HOURS
2 fl. oz. (59mL)

PATENTED FORMULA